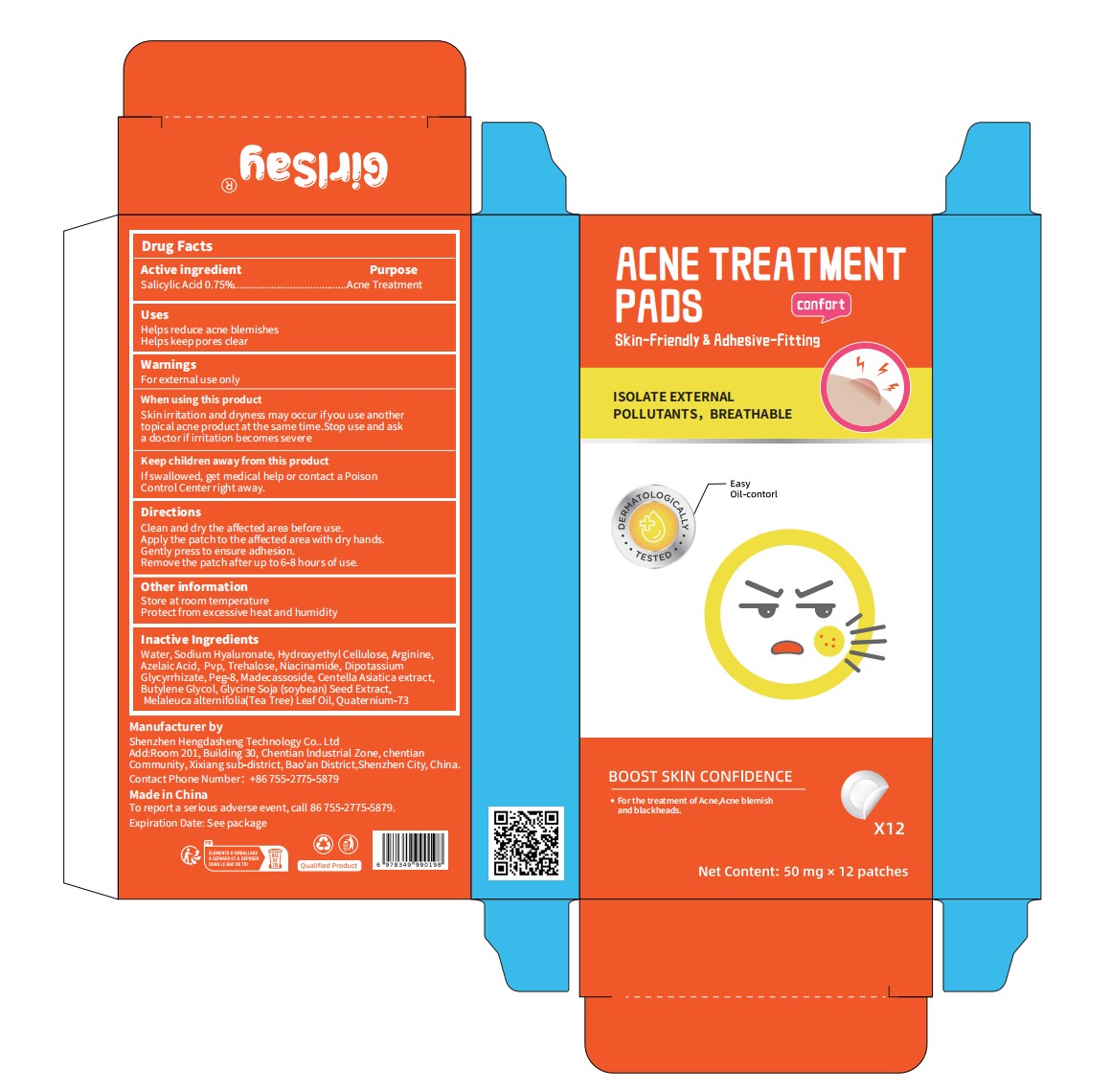 DRUG LABEL: ACNE TREATMENT PADS
NDC: 87308-001 | Form: PATCH
Manufacturer: Shenzhen Hengdasheng Technology Co., Ltd
Category: otc | Type: HUMAN OTC DRUG LABEL
Date: 20260117

ACTIVE INGREDIENTS: SALICYLIC ACID 0.75 U/100 U
INACTIVE INGREDIENTS: QUATERNIUM-73; WATER; SODIUM HYALURONATE; HYDROXYETHYLCELLULOSE; ARGININE; AZELAIC ACID; PVP; TREHALOSE; NIACINAMIDE; DIPOTASSIUM GLYCYRRHIZATE; PEG-8; MADECASSOSIDE; CENTELLA ASIATICA TRITERPENOIDS; BUTYLENE GLYCOL; GLYCINE SOJA (SOYBEAN) SEED; MELALEUCA ALTERNIFOLIA (TEA TREE) LEAF OIL

87308-001

Active Ingredient(s)

Salicylic acid 0.75%

Purpose

Acne Treatment

Use

Helps reduce acne blemishes

Helps keep pores clear

Warnings

For external use only

Do not use

If you are allergic to this product, please do not use it.

WHEN USING

Skin irritation and dryness may occur if you use anothertopical acne product at the same time.Stop use and aska doctor if irritation becomes severe

If there is irritation, stop using it immediately.

KEEP OUT OF REACH OF CHILDREN

If swallowed, get medical help or contact a PoisonControl Center right away.

Directions

Clean and dry the affected area before use.
Apply the patch to the affected area with dry hands.
Gently press to ensure adhesion.
Remove the patch after up to 6-8 hours of use.

Other information

Store at room temperature

Protect from excessive heat and humidity

Inactive ingredients

Water, Sodium Hyaluronate, Hydroxyethyl Cellulose, Arginine,Azelaic Acid, Pvp, Trehalose, Niacinamide, DipotassiumGlycyrrhizate, Peg-8, Madecassoside, Centella Asiatica extract,Butylene Glycol, Glycine Soja (soybean) Seed Extract,Melaleuca alternifolia(Tea Tree) Leaf Oil,Quaternium-73